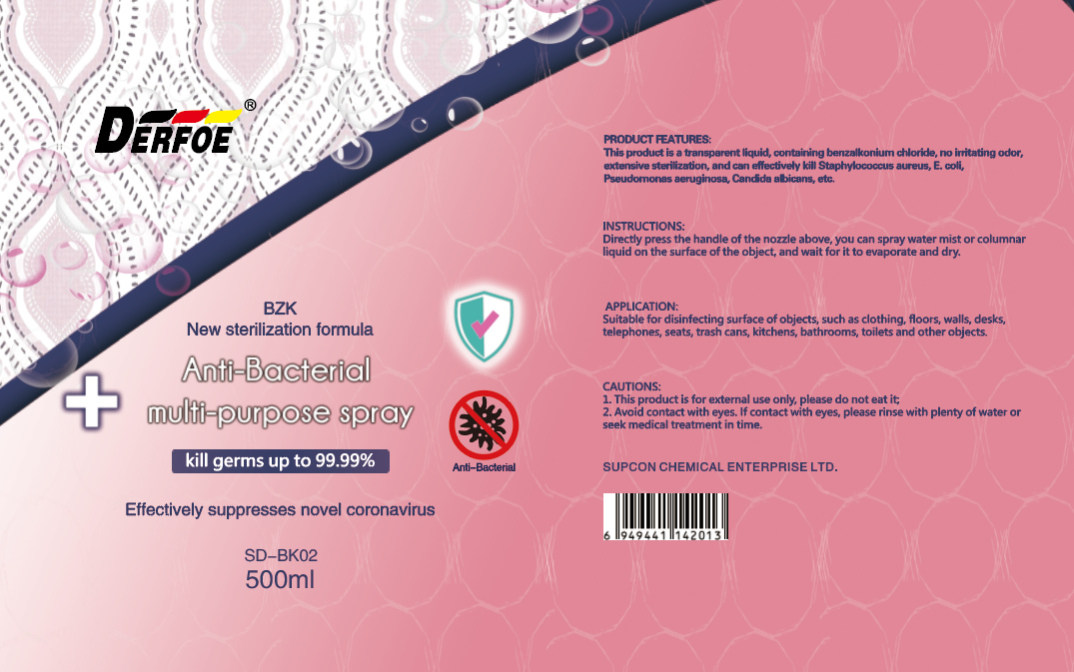 DRUG LABEL: BZK NEW STERILIZATION FORMULA AITI-BACTERIAL MULTI-PURPOSESPRAY
NDC: 55475-002 | Form: LIQUID
Manufacturer: Supcon Advanced Materials Technology Co., Ltd.
Category: otc | Type: HUMAN OTC DRUG LABEL
Date: 20200513

ACTIVE INGREDIENTS: BENZALKONIUM CHLORIDE 1 g/500 mL
INACTIVE INGREDIENTS: WATER; MENTHA SPICATA OIL

DOSAGE AND ADMINISTRATION

Room temperature storage

INACTIVE INGREDIENT

Pure water and Additive

INDICATIONS AND USAGE

Directly press the handle of the nozzle above, you can spray water mist or columnar liquid on the surface of the object, and wait for it to evaporate and dry.

ACTIVE INGREDIENT

Benzalkonium chloride

keep out of reach of children

PURPOSE

Disinfection
Sterilization
No Rinseing

WARNINGS

1. This product is for external use only, please do not eat it
2. Avoid contact with eyes. if contact with eyes, please rinse with plenty of water or seek medical treatment in time.